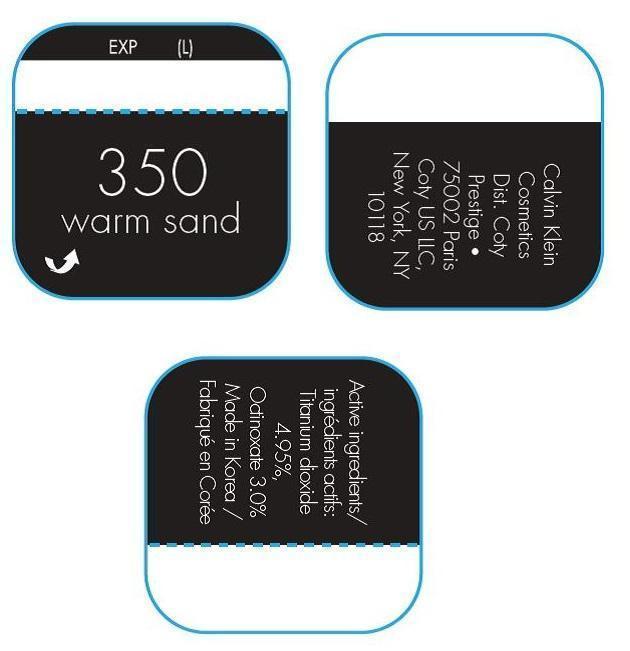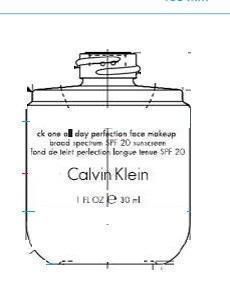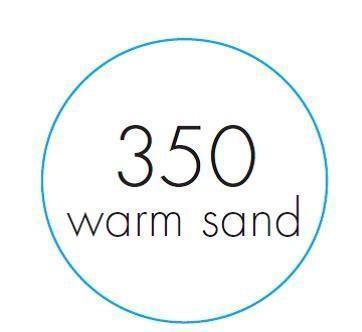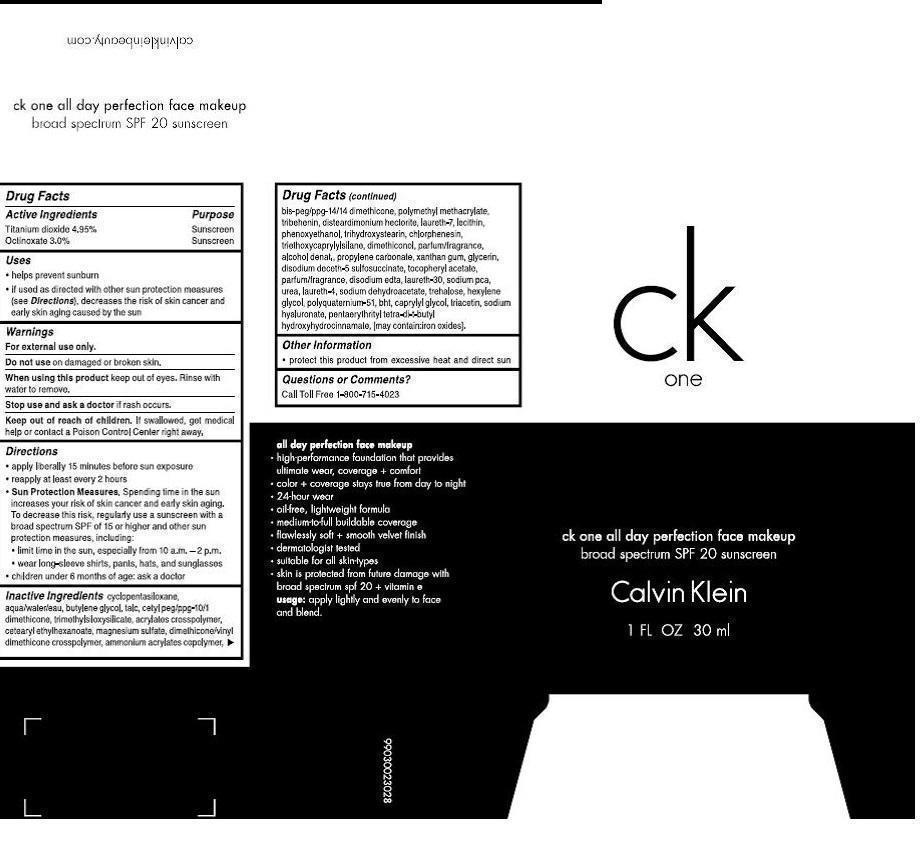 DRUG LABEL: ck one all day perfection face makeup
NDC: 66184-530 | Form: LOTION
Manufacturer: Coty US LLC
Category: otc | Type: HUMAN OTC DRUG LABEL
Date: 20140527

ACTIVE INGREDIENTS: Titanium Dioxide 1.648359 g/30 mL; Octinoxate  0.999 g/30 mL
INACTIVE INGREDIENTS: Water; BUTYLENE GLYCOL; TALC; CETYL PEG/PPG-10/1 DIMETHICONE (HLB 2); TRIMETHYLSILOXYSILICATE (M/Q 0.6-0.8); CETEARYL ETHYLHEXANOATE; MAGNESIUM SULFATE; DIMETHICONE/VINYL DIMETHICONE CROSSPOLYMER (HARD PARTICLE); POLY(METHYL METHACRYLATE; 450000 MW); TRIBEHENIN; DISTEARDIMONIUM HECTORITE; LAURETH-7; EGG PHOSPHOLIPIDS; PHENOXYETHANOL; TRIHYDROXYSTEARIN; CHLORPHENESIN; TRIETHOXYCAPRYLYLSILANE; DIMETHICONOL (100000 CST); PROPYLENE CARBONATE; XANTHAN GUM; GLYCERIN; .ALPHA.-TOCOPHEROL ACETATE; EDETATE DISODIUM; LAURETH-30; SODIUM PYRROLIDONE CARBOXYLATE; UREA; LAURETH-4; SODIUM DEHYDROACETATE; TREHALOSE; HEXYLENE GLYCOL; POLYQUATERNIUM-51 (2-METHACRYLOYLOXYETHYL PHOSPHORYLCHOLINE/N-BUTYL METHACRYLATE; 3:7); BUTYLATED HYDROXYTOLUENE; CAPRYLYL GLYCOL; TRIACETIN; HYALURONATE SODIUM

Drug Facts

Active Ingredients

Titanium Dioxide 4.95%

Octinoxate 3.0%

Purpose

Titanium Dioxide}Sunscreen

Octinoxate}Sunscreen

Keep out of reach of children. If swallowed, get medical help or contact a Poison Control Center right away.

Uses

- Helps prevent sunburn.
- If used as directed with other sun protection measures (see Directions), decreases the risk of skin cancer and early skin aging caused by the sun.

Warnings

For external use only.

Do not use on damaged or broken skin.

When using this product keep out of eyes. Rinse with water to remove.

Stop use and ask a doctor if rash occurs.

Directions

- Apply liberally 15 minutes before sun exposure
- Reapply at least every 2 hours
- Sun protection measures. Spending time in the sun increases your risk of skin cancer and early skin aging. To deacrease this risk, regularly use a sunscreen with a broad spectrum of SPF of 15 or higher and other sun protection measures including:
- limit time in the sun, especially from 10 a.m. -2p.m.
- wear long-sleeve shirts, pants, hats and sunglasses
- Children under 6 months: ask a doctor

Inactive Ingredients

Cyclopentasiloxane, Aqua/Water/Eau, Butylene Glycol, Talc, Cetyl PEG/PPG-10/1 Dimethicone, Trimethylsiloxysilicate, Acrylates Crosspolymer, Ammonium Acrylates Copolymer, BIS-PEG/PPG-14/14 Dimethicone, Polymethyl Methacrylate, Tribehenin, Disteardimonium Hectorite, Laureth-7, Lecithin, Phenoxyethanol, Trihydroxystearin, Chlorphenesin, Triethoxycaprylsilane, Dimethiconol, Parfum/Fragrance, Alcohol Denat., Propylene Carbonate, Xanthan Gum, Glycerin, Disodium Deceth-5 Sulfosuccinate, Tocopheryl Acetate, Parfum/Fragrance, Disodium EDTA, Laureth-30, Sodium PCA, Urea, Laurthe-4, Sodium Dehydroacetate, Trehalose, Hexylene Glycol, Polyquaternium-51, BHT, Caprylyl Glycol, Triacetin, Sodium Hyaluronate, Pentaerythrityl Tetra-Di-T-Butyl Hydroxyhydrocinnamate, [May Contain: Iron Oxides].